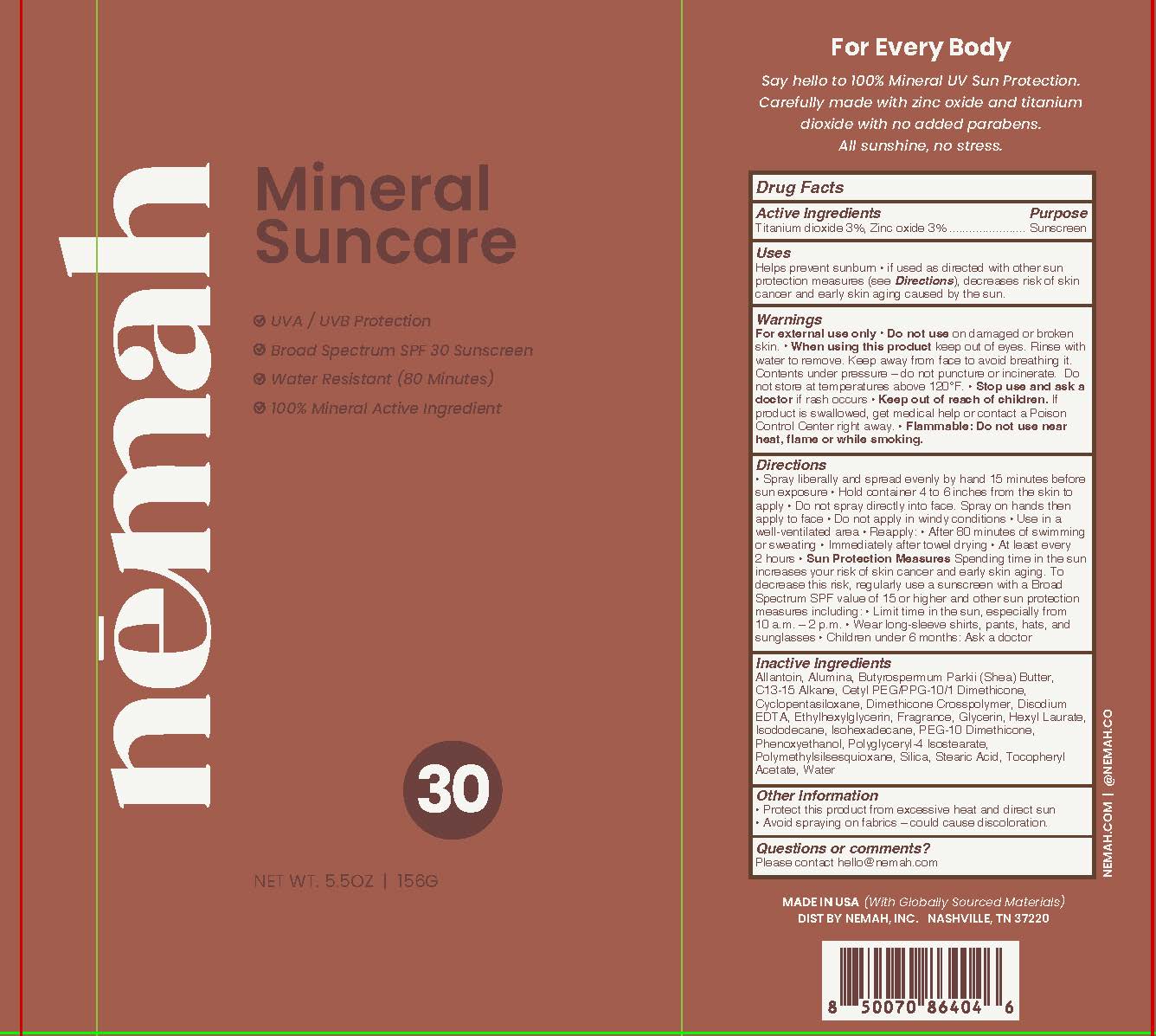 DRUG LABEL: Nemah SPF 30 Mineral C/S
NDC: 85721-0001 | Form: AEROSOL
Manufacturer: Nemah, Inc.
Category: otc | Type: HUMAN OTC DRUG LABEL
Date: 20250605

ACTIVE INGREDIENTS: TITANIUM DIOXIDE 0.03 g/1 g; ZINC OXIDE 0.03 g/1 g
INACTIVE INGREDIENTS: ALUMINA; GLYCERIN; ISOHEXADECANE; ISODODECANE; .ALPHA.-TOCOPHEROL ACETATE; ETHYLHEXYLGLYCERIN; HEXYL LAURATE; PHENOXYETHANOL; CETYL PEG/PPG-10/1 DIMETHICONE (HLB 5); ALLANTOIN; CYCLOPENTASILOXANE; DIMETHICONE CROSSPOLYMER; PEG-10 DIMETHICONE (500 CST); SILICA; STEARIC ACID; WATER; C13-15 ALKANE; BUTYROSPERMUM PARKII (SHEA) BUTTER; EDETATE DISODIUM; POLYGLYCERYL-4 ISOSTEARATE; POLYMETHYLSILSESQUIOXANE (11 MICRONS)

Nemah SPF 30 Mineral Continuous Spray

Active ingredients

Titanium Dioxide 3%

Zinc Oxide 3%

Purpose

Sunscreen

Uses

- helps prevent sunburn
- if used as directed with other sun protection measures (see Directions), decreases risk of skin cancer and early skin aging caused by the sun

Warnings

- For external use only
- Contents under pressure - do not puncture or incinerate. Do not store at temperatures above 120F
- Flammable: Do not use near heat, flame or while smoking

Do not use

on damaged or broken skin

When using this product

keep out of eyes. Rinse with water to remove. Keep away from face to avoid breathing it.

Stop use and ask a doctor

if rash occurs

Keep out of reach of children.

If product is swallowed, get medical help or contact a Poison Control Center right away.

Directions

- spray liberally and spread evenly by hand 15 minutes before sun exposure.
- Hold container 4 to 6 inches from the skin to apply
- Do not spray directly into face. Spray on hands then apply to face
- Do not apply in windy conditions.
- Use in a well-ventilated area
- Reapply:
- after 80 minutes of swimming or sweating
- immediately after towel drying
- at least every 2 hours
- Sun Protection Measures. Spending time in the sun increases your risk of skin cancer and early skin aging. To decrease this risk, regularly use a sunscreen with a Broad Spectrum SPF value of 15 or higher and other sun protection measures including:
- Limit time in the sun, especially from 10 am - 2 pm
- Wear long-sleeve shirts, pants, hats, and sunglasses
- Children under 6 months: ask a doctor

Inactive ingredients

Allantoin, Alumina, Butyrospermum Parkii (Shea) Butter, C13-15 Alkane, Cetyl PEG/PPG-10/1 Dimethicone, Cyclopentasiloxane, Dimethicone Crosspolymer, Disodium EDTA, Ethylhexylglycerin, Fragrance, Glycerin, Hexyl Laurate, Isododecane, Isohexadecane, PEG-10 Dimethicone, Phenoxyethanol, Polyglyceryl-4 Isostearate, Polymethylsilsesquioxane, Silica, Stearic Acid, Tocopheryl Acetate, Water

Other Information

- protect this product from excessive heat and direct sun
- avoid spraying on fabrics - could cause discoloration

Questions or comments?

Please contact hello@nemah.com